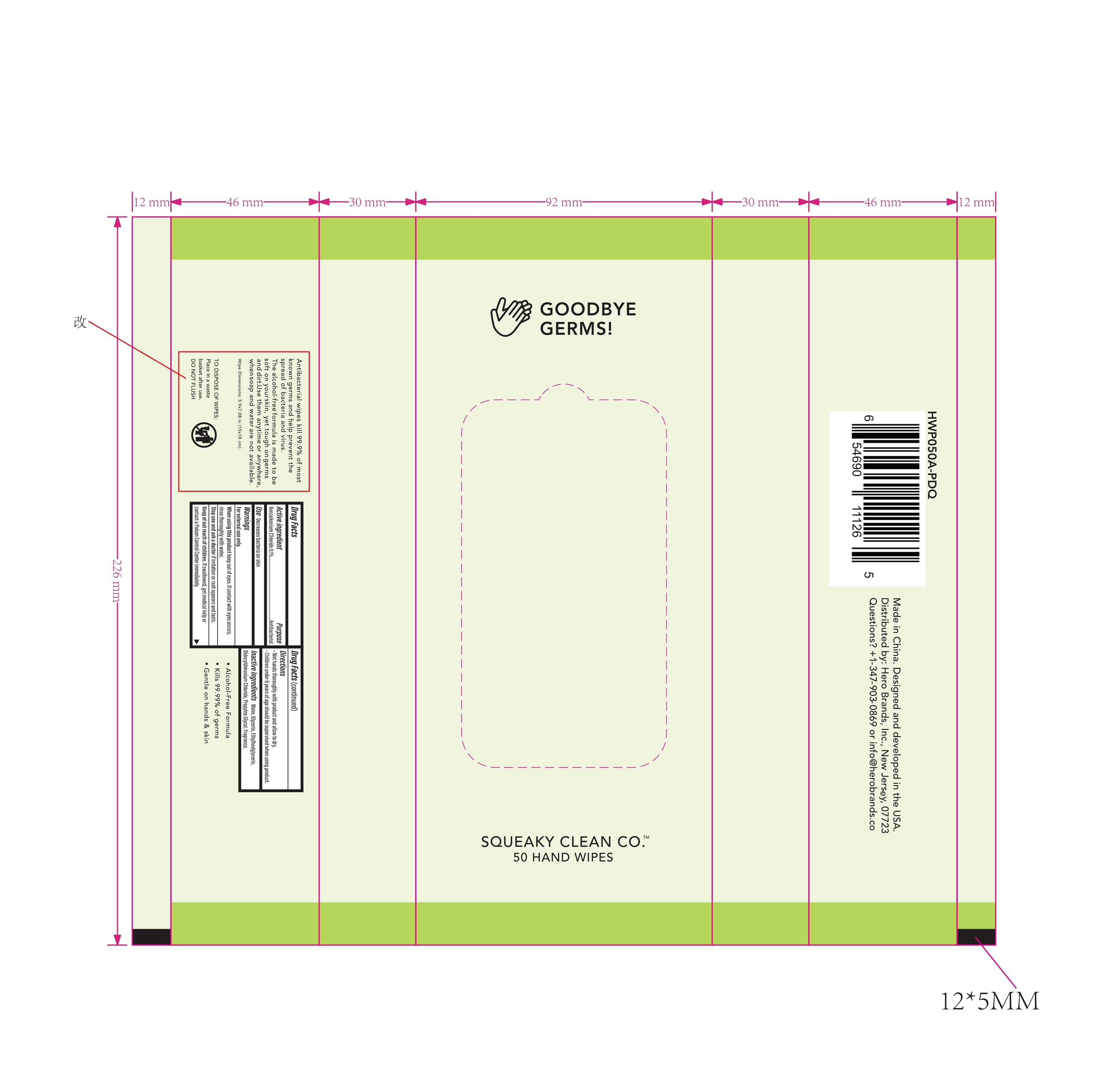 DRUG LABEL: Wet Wipes
NDC: 75662-050 | Form: CLOTH
Manufacturer: Ningbo Chenxing Daily Necessities Co., Ltd.
Category: otc | Type: HUMAN OTC DRUG LABEL
Date: 20200816

ACTIVE INGREDIENTS: BENZALKONIUM CHLORIDE 0.1 g/100 g
INACTIVE INGREDIENTS: ALOE; GLYCERIN; ETHYLHEXYLGLYCERIN; WATER; PROPYLENE GLYCOL; DIDECYLDIMONIUM CHLORIDE

75662-050 Wet Wipes/BENZALKONIUM CHLORIDE Ningbo Chenxing Daily Necessities Co., Ltd.

Active Ingredient(s)

Benzalkonium Chloride 0.1%. Purpose: Antibacterial

Purpose

Antibacterial, Hand Wipes

Use

Decreases bacteria on skin.

Warnings

- For external use only.

Do not use

if you are allergic to any of the ingredients.
on children less than 2 years of age unless directed by a doctor.
as a diaper wipe or for personal cleaning

When using this product keep out of eyes, If contact with eyes occurs, rinse thoroughly with water.

Stop use and ask a doctor if irritation or rash appears and lasts.

Keep out of reach of children. If swallowed, get medical help or contact a Poison Control Center immediately.

Directions

- Wet hand thoroughly with product and allow to dry.
  - Children under 6 years of age should be supervised when using product.

Other information

Keep containers tightly closed in a dry, cool and well-ventilated place.

Recommended storage temperature: 0℃ to 40℃.

Kill 99% of germs that may cause illness in just 5 minutes.

Inactive ingredients

Water,Glycerin, Ethylhexlglycerin, Didecyldimonium Chloride, Propylne Glycol, Fragrance.

Package Label - Principal Display Panel

50 Hand Wipes NDC:75662-050-50